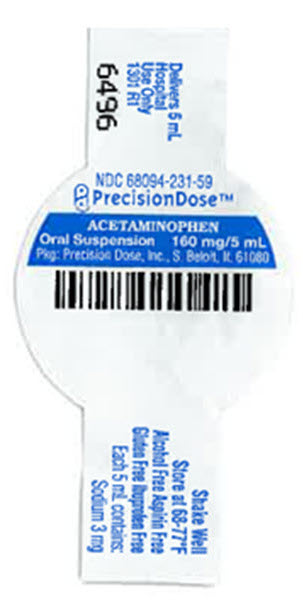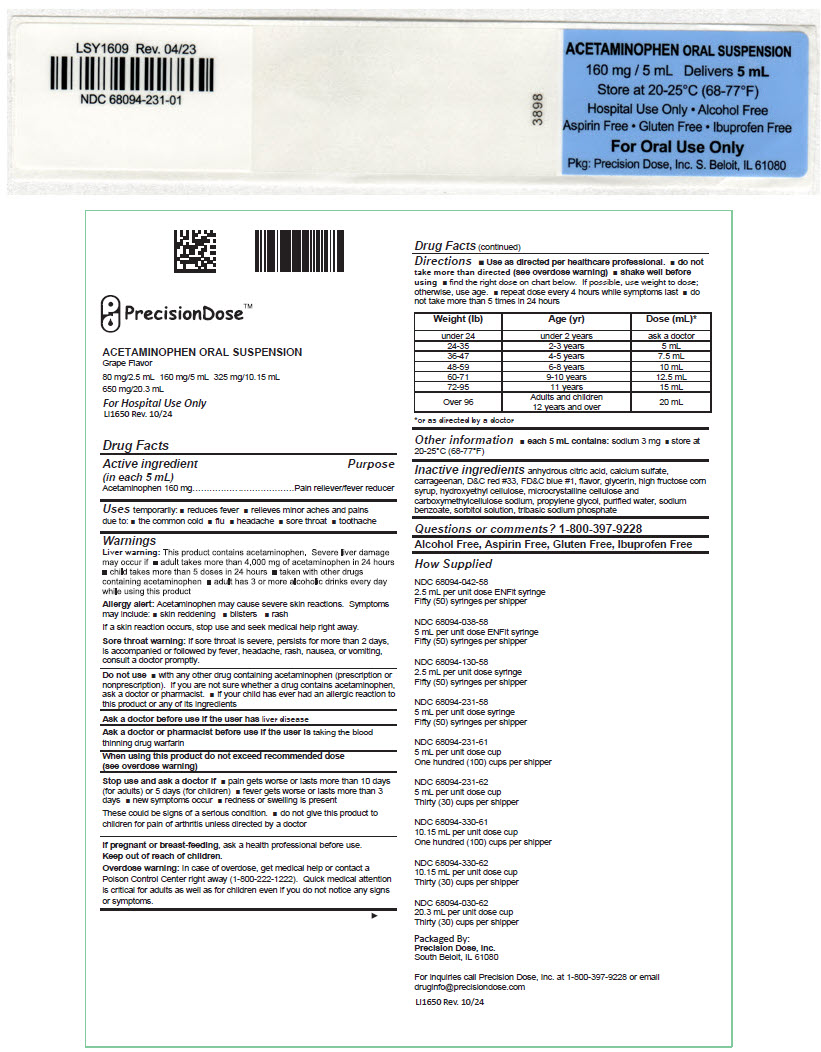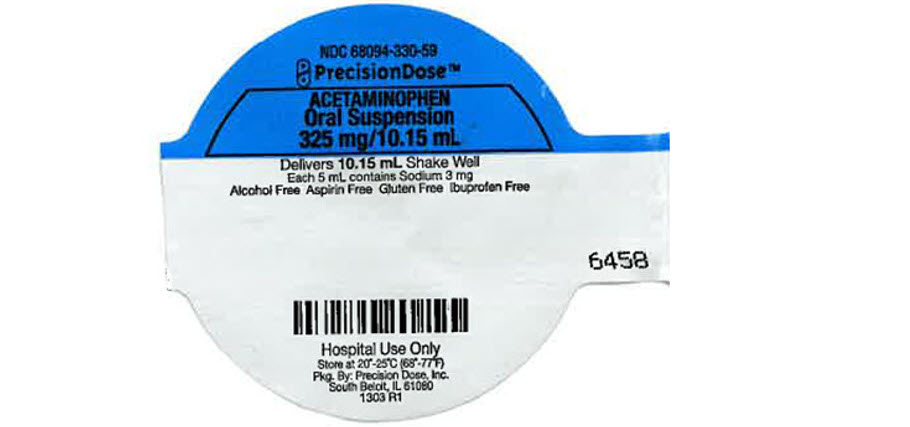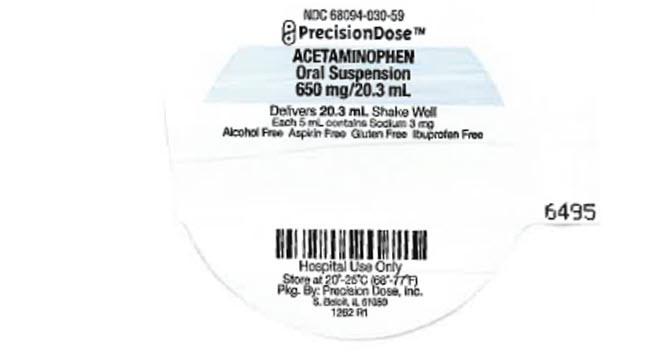 DRUG LABEL: Acetaminophen
NDC: 68094-231 | Form: SUSPENSION
Manufacturer: Precision Dose, Inc.
Category: otc | Type: HUMAN OTC DRUG LABEL
Date: 20250829

ACTIVE INGREDIENTS: Acetaminophen 160 mg/5 mL
INACTIVE INGREDIENTS: anhydrous citric acid; butylparaben; calcium sulfate, unspecified form; carrageenan; D&C red no. 33; FD&C blue no. 1; glycerin; high fructose corn syrup; microcrystalline cellulose; CARBOXYMETHYLCELLULOSE SODIUM, UNSPECIFIED; propylene glycol; water; sodium benzoate; sorbitol; sodium phosphate, tribasic

ACETAMINOPHEN ORAL SUSPENSION

Grape Flavor

80 mg/2.5 mL 160 mg/5 mL 325 mg/10.15 mL

650 mg/20.3 mL

For Hospital Use Only

LI1650 Rev. 10/24

Drug Facts

Active ingredient (in each 5 mL)

Acetaminophen 160 mg

Purpose

Pain reliever/fever reducer

Uses

temporarily:

- reduces fever
- relieves minor aches and pains due to:
- the common cold
- flu
- headache
- sore throat
- toothache

Warnings

Liver warning

This product contains acetaminophen. Severe liver damage may occur if

- adult takes more than 4,000 mg of acetaminophen in 24 hours
- child takes more than 5 doses in 24 hours
- taken with other drugs containing acetaminophen
- adult has 3 or more alcoholic drinks every day while using this product

Allergy alert

Acetaminophen may cause severe skin reactions. Symptoms may include:

- skin reddening
- blisters
- rash

If a skin reaction occurs, stop use and seek medical help right away.

Sore throat warning

If sore throat is severe, persists for more than 2 days, is accompanied or followed by fever, headache, rash, nausea, or vomiting, consult a doctor promptly.

Do not use

- with any other drug containing acetaminophen (prescription or nonprescription). If you are not sure whether a drug contains acetaminophen, ask a doctor or pharmacist.
- if your child has ever had an allergic reaction to this product or any of its ingredients

Ask a doctor before use if the user has liver disease

Ask a doctor or pharmacist before use if the user is taking the blood thinning drug warfarin

When using this product do not exceed recommended dose (see overdose warning)

Stop use and ask a doctor if

- pain gets worse or lasts more than 10 days (for adults) or 5 days (for children)
- fever gets worse or lasts more than 3 days
- new symptoms occur
- redness or swelling is present

These could be signs of a serious condition.

- do not give this product to children for pain of arthritis unless directed by a doctor

PREGNANCY OR BREAST FEEDING

If pregnant or breast-feeding, ask a health professional before use.

Keep out of reach of children.

Overdose warning

In case of overdose, get medical help or contact a Poison Control Center right away (1-800-222-1222). Quick medical attention is critical for adults as well as for children even if you do not notice any signs or symptoms.

Directions

- Use as directed per healthcare professional.
- do not take more than directed (see overdose warning)
- shake well before using
- find the right dose on chart below. If possible, use weight to dose; otherwise, use age.
- repeat dose every 4 hours while symptoms last
- do not take more than 5 times in 24 hours

Weight (lb) | Age (yr) | Dose (mL) [or as directed by a doctor]
under 24 | under 2 years | ask a doctor
24-35 | 2-3 years | 5 mL
36-47 | 4-5 years | 7.5 mL
48-59 | 6-8 years | 10 mL
60-71 | 9-10 years | 12.5 mL
72-95 | 11 years | 15 mL
Over 96 | Adults and children 12 years and over | 20 mL

Other information

- each 5 mL contains: sodium 3 mg
- store at 20-25°C (68-77°F)

Inactive ingredients

anhydrous citric acid, calcium sulfate, carrageenan, D&C red #33, FD&C blue #1, flavor, glycerin, high fructose corn syrup, hydroxyethyl cellulose, microcrystalline cellulose and carboxymethylcellulose sodium, propylene glycol, purified water, sodium benzoate, sorbitol solution, tribasic sodium phosphate

Questions or comments?

1-800-397-9228

Alcohol Free, Aspirin Free, Gluten Free, Ibuprofen Free

How Supplied

NDC 68094-042-58
2.5 mL per unit dose ENFit syringe
Fifty (50) syringes per shipper

NDC 68094-038-58
5 mL per unit dose ENFit syringe
Fifty (50) syringes per shipper

NDC 68094-130-58
2.5 mL per unit dose syringe
Fifty (50) syringes per shipper

NDC 68094-231-58
5 mL per unit dose syringe
Fifty (50) syringes per shipper

NDC 68094-231-61
5 mL per unit dose cup
One hundred (100) cups per shipper

NDC 68094-231-62
5 mL per unit dose cup
Thirty (30) cups per shipper

NDC 68094-330-61
10.15 mL per unit dose cup
One hundred (100) cups per shipper

NDC 68094-330-62
10.15 mL per unit dose cup
Thirty (30) cups per shipper

NDC 68094-030-62
20.3 mL per unit dose cup
Thirty (30) cups per shipper

Packaged By:
Precision Dose, Inc.
South Beloit, IL 61080

For inquiries call Precision Dose, Inc. at 1-800-397-9228 or email druginfo@precisiondose.com

LI1650 Rev. 10/24

PRINCIPAL DISPLAY PANEL - 5 mL Cup Label

NDC 68094-231-59

PrecisionDose™

ACETAMINOPHEN
Oral Suspension
160 mg/5 mL

Pkg: Precision Dose, Inc., S. Beloit, IL 61080

PRINCIPAL DISPLAY PANEL - 5 mL Syringe Label

ACETAMINOPHEN ORAL SUSPENSION

160 mg / 5 mL
Delivers 5 mL

Store at 20-25°C (68-77°F)

Hospital Use Only • Alcohol Free

Aspirin Free • Gluten Free • Ibuprofen Free

For Oral Use Only

Pkg: Precision Dose, Inc. S. Beloit, IL 61080

PRINCIPAL DISPLAY PANEL - 10.15 mL Cup Label

NDC 68094-330-59

PrecisionDose™

ACETAMINOPHEN
Oral Suspension
325 mg/10.15 mL

Delivers 10.15 mL
Shake Well
Each 5 mL contains Sodium 3 mg
Alcohol Free
Aspirin Free
Gluten Free
Ibuprofen Free

Hospital Use Only
Store at 20°-25°C (68°-77°F)
Pkg. By: Precision Dose, Inc.
South Beloit, IL 61080
1303 R1

PRINCIPAL DISPLAY PANEL - 20.3 mL Cup Label

NDC 68094-030-59

PrecisionDose™

ACETAMINOPHEN
Oral Suspension
650 mg/20.3 mL

Delivers 20.3 mL Shake Well
Each 5 mL contains Sodium 3 mg
Alcohol Free Aspirin Free Gluten Free Ibuprofen Free

Hospital Use Only
Store at 20°-25°C (68°-77°F)
Pkg. By: Precision Dose, Inc.
S. Beloit, IL 61080
1262 R1